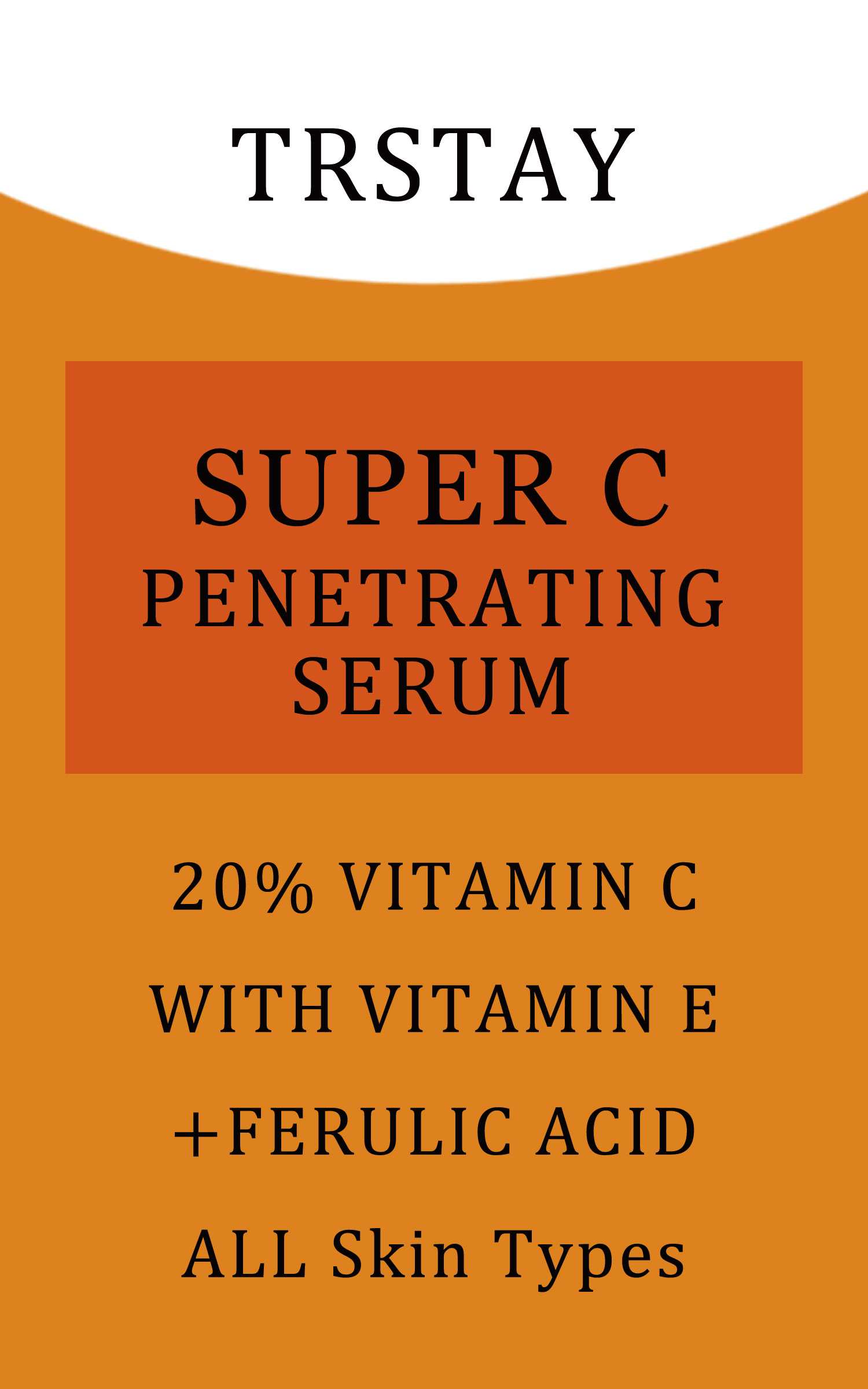 DRUG LABEL: Super C Penetrating Serum
NDC: 84894-047 | Form: LIQUID
Manufacturer: YiwuZhixinTradeCoLtd
Category: otc | Type: HUMAN OTC DRUG LABEL
Date: 20250112

ACTIVE INGREDIENTS: NIACINAMIDE 5 g/100 mL
INACTIVE INGREDIENTS: PALMITOYL TRIPEPTIDE-1; CHLORPHENESIN; SESAME OIL; PALMITOYL PENTAPEPTIDE-4; GLYCERIN

COMPONENTS

Salicylic acid 2%

PURPOSE

wart remover

INDICATIONS AND USAGE

Apply twice daly(moring and night as a man and once as a woman.Afer apicaion, proeed with an acive masage for 3-5 minutes unthe product is fuy absorbed

WARNINGS

Forevemaluseony Avoid coniac wth eves li coniac ocus nse ihorouthly wt waier Keep out ofreach oi chidrenifvou ale preanant.nursing. otiaveanyunderving medca condion.consutyou healthcare provider before using the product

DOSAGE AND ADMINISTRATION

For external use only.

DO NOT USE

Discontinue use if any irritation or adverse reaction occurs

When using this product, avoid contact with eyes. lf contact occurs, rinse thoroughly with waterDiscontinue use if any irritation or adverse reaction occurs.

STOP USE

on broken or irritated scalp

KEEP OUT OF REACH OF CHILDREN

If sxralowed, get medical help or contact a Poison Conirol Cenler ngiht away.

INACTIVE INGREDIENT

Acrylates copolymer, Ethyl acetate